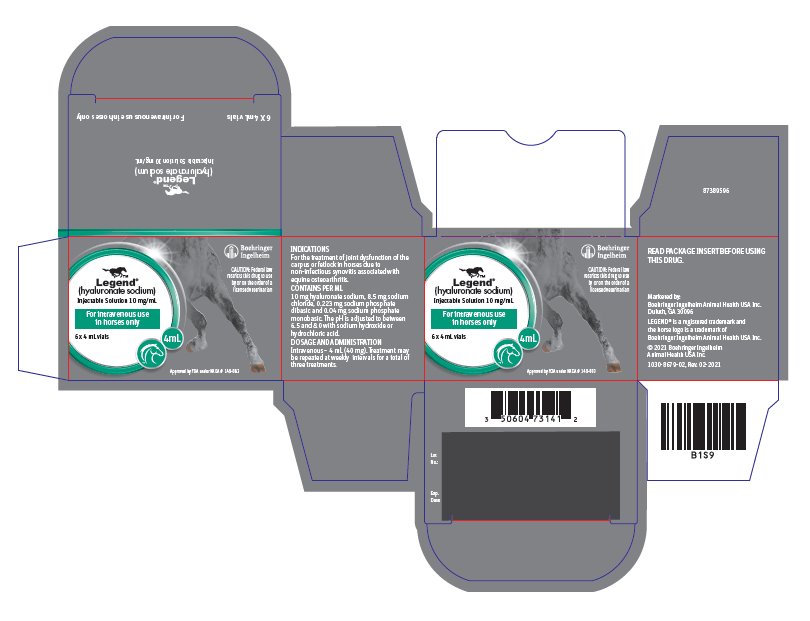 DRUG LABEL: Legend
NDC: 0010-3141 | Form: INJECTION, SOLUTION
Manufacturer: Boehringer Ingelheim Animal Health USA Inc
Category: animal | Type: PRESCRIPTION ANIMAL DRUG LABEL
Date: 20250502

ACTIVE INGREDIENTS: hyaluronate sodium 10 mg/1 mL
INACTIVE INGREDIENTS: Sodium Chloride 8.5 mg/1 mL; SODIUM PHOSPHATE, DIBASIC, UNSPECIFIED FORM 0.223 mg/1 mL; SODIUM PHOSPHATE, MONOBASIC, UNSPECIFIED FORM 0.04 mg/1 mL

Legend®
(hyaluronate sodium)
Injectable Solution

For intravenous use in horses only

4 mL

CAUTION:

Federal law restricts this drug to use by or on the order of a licensed veterinarian.

DESCRIPTION:

LEGEND Injectable Solution is a clear, colorless solution of low viscosity. LEGEND Injectable Solution is pyrogen free, sterile and does not contain a preservative. It is administered by intravenous injection.

Hyaluronic acid, the conjugate acid of hyaluronate sodium, is extracted from the capsule of Streptococcus spp. and purified, resulting in a form which is essentially free of protein and nucleic acids.

LEGEND Injectable Solution is supplied in 4 mL (40 mg) vials. Each mL contains 10 mg hyaluronate sodium, 8.5 mg sodium chloride, 0.223 mg sodium phosphate dibasic, and 0.04 mg sodium phosphate monobasic. The pH is adjusted to between 6.5 and 8.0 with sodium hydroxide or hydrochloric acid.

CHEMISTRY:

Hyaluronic acid, a glycosaminoglycan, can exist in the following forms depending upon the chemical environment in which it is found: as the acid, hyaluronic acid; as the sodium salt, sodium hyaluronate (hyaluronate sodium); or as the hyaluronate anion. These terms may be used interchangeably but in all cases, reference is made to the glycosaminoglycan composed of repeating subunits of D-glucuronic acid and N-acetyl-D-glucosamine linked together by glycosidic bonds. Since this product originates from a microbial source, there is no potential for contamination with dermatan or chondroitin sulfate or any other glycosaminoglycan.

CLINICAL PHARMACOLOGY:

Hyaluronic acid is a naturally occurring substance present in connective tissue, skin, vitreous humour and the umbilical cord in all mammals. High concentrations of hyaluronic acid are also found in the synovial fluid. It also constitutes the major component of the capsule of certain microorganisms. The hyaluronic acid produced by bacteria is of the same structure and configuration as that found in mammals.

The actual mechanism of action for hyaluronate sodium in the healing of degenerative joint disease is not completely understood. One major function appears to be the regulation of normal cellular constituents. This effect decreases the impact of exudation, enzyme release and subsequent degradation of joint integrity. Additionally, hyaluronate sodium exerts an anti-inflammatory action by inhibiting the movement of granulocytes and macrophages.^1

Hyaluronate molecules are long chains which form a filter network interspersed with normal cellular fluids. It is widely accepted that injection directly into the joint pouch enhances the healing of inflamed synovium by restoring lubrication of the joint fluid. This further supplements the visco-elastic properties of normal joint fluid.

INDICATIONS:

LEGEND Injectable Solution is indicated in the treatment of joint dysfunction of the carpus or fetlock in horses due to non-infectious synovitis associated with equine osteoarthritis.

DOSAGE AND ADMINISTRATION:

4 mL (40 mg) injected intravenously. Treatment may be repeated at weekly intervals for a total of three treatments.

Use aseptic technique and inject slowly into the jugular vein.

Horses should be given stall rest after treatment before gradually resuming normal activity.

Discard any unused portion of the drug and empty vial after opening.

CONTRAINDICATIONS:

There are no known contraindications for the use of LEGEND Solution in horses.

RESIDUE WARNING:

Do not use in horses intended for human consumption.

HUMAN WARNINGS:

Not for use in humans. Keep this and all other drugs out of reach of children.

WARNINGS

ANIMAL SAFETY WARNING:

Not for Intra-articular use.

PRECAUTIONS:

Radiographic evaluation should be carried out in cases of acute lameness to ensure that the joint is free from serious fracture.

The safety of LEGEND Injectable Solution has not been evaluated in breeding stallions or in breeding, pregnant or lactating mares.

ADVERSE REACTIONS:

No local or systemic side effects were observed in the field studies using LEGEND Injectable Solution.

Post-Approval Experience: While all adverse reactions are not reported, the following adverse reactions are based on voluntary post-approval reporting for LEGEND Injectable Solution: Occasional depression, lethargy, and fever.

To report suspected adverse events, for technical assistance or to obtain a copy of the Safety Data Sheet (SDS), contact Boehringer Ingelheim Animal Health USA Inc. at 1-888-637-4251. For additional information about adverse drug experience reporting for animal drugs, contact FDA at 1-888-FDA-VETS or online at www.fda.gov/reportanimalae.

EFFECTIVENESS:

Forty-six horses with lameness in either the carpal or fetlock joints were treated intravenously or intra-articularly with LEGEND Injectable Solution in a well-controlled field study conducted at four locations. One, two or three injections were given based on clinical improvement. Overall clinical improvement was judged as excellent or good in 90% of the cases treated intravenously and 96% of those treated intra-articularly with LEGEND Injectable Solution.

ANIMAL SAFETY:

LEGEND Injectable Solution was administered to normal horses at one, three and five times the recommended intra-articular dosage of 20 mg and intravenous dosage of 40 mg. Treatments were given once weekly for nine consecutive weeks (three times the maximum duration). No systemic clinical signs were observed nor were there any adverse effects upon hematology or clinical chemistry parameters. A transient, slight to mild post injection swelling of the joint capsule occurred in some of the animals treated intra-articularly with LEGEND Injectable Solution as it did in the saline treated control horse. No gross or histological lesions were observed in the soft tissues or the surface areas of the treated joint.

STORAGE:

Store at or below 77°F (25°C). Brief excursions to 104°F (40°C) are permitted.

HOW SUPPLIED:

LEGEND Injectable Solution is supplied in a carton of six 4 mL (40 mg) bottles.

Approved by FDA under NADA # 140-883

Marketed by: Boehringer Ingelheim Animal Health USA Inc., Duluth, GA 30096

REFERENCES

REFERENCE:

^1Swanstrom, O.G. 1978. Hyaluronate (hyaluronic acid) and its use, Proc. American Assoc. Equine Pract., 24th annual convention, pp. 345-348.

® LEGEND is a registered trademark and the horse logo is a trademark of

Boehringer Ingelheim Animal Health USA Inc.

© 2019 Boehringer Ingelheim Animal Health USA Inc.

1050-8682-03, Rev. 12-2019

86851091

PRINCIPAL DISPLAY PANEL - 4 mL Vial Carton

Legend®
(hyaluronate sodium)
Injectable Solution 10 mg/mL

For intravenous use in horses only

6 x 4 mL vials

CAUTION: Federal law restricts this drug to use by or on the order of a licensed veterinarian.

Approved by FDAunderNADA # 140-883